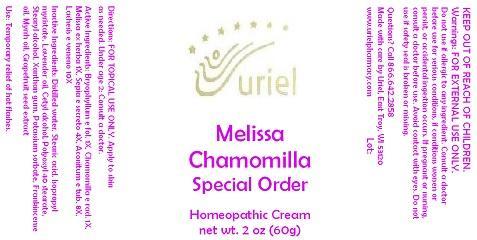 DRUG LABEL: Melissa Chamomilla Special Order
NDC: 48951-7028 | Form: CREAM
Manufacturer: Uriel Pharmacy Inc.
Category: homeopathic | Type: HUMAN OTC DRUG LABEL
Date: 20140920

ACTIVE INGREDIENTS: KALANCHOE DAIGREMONTIANA LEAF 1 [hp_X]/1 g; MATRICARIA RECUTITA 1 [hp_X]/1 g; MELISSA OFFICINALIS 1 [hp_X]/1 g; SEPIA OFFICINALIS JUICE 4 [hp_X]/1 g; ACONITUM NAPELLUS 8 [hp_X]/1 g; LACHESIS MUTA VENOM 10 [hp_X]/1 g
INACTIVE INGREDIENTS: WATER; STEARIC ACID; ISOPROPYL MYRISTATE; LAVENDER OIL; CETYL ALCOHOL; POLYOXYL 40 STEARATE; STEARYL ALCOHOL; XANTHAN GUM; POTASSIUM SORBATE; FRANKINCENSE OIL; MYRRH OIL; CITRUS PARADISI SEED

Melissa Chamomilla Special Order

INDICATIONS AND USAGE

Directions: FOR TOPICAL USE ONLY.

DOSAGE AND ADMINISTRATION

Apply to skin as needed. Under age 2: Consult a doctor.

ACTIVE INGREDIENT

Active Ingredients: Bryophyllum e fol. 1X, Chamomilla e rad. 1X, Melissa ex herba 1X, Sepia e secreto 4X, Aconitum e tub. 8X, Lachesis e veneno 10X

INACTIVE INGREDIENT

Inactive Ingredients: Distilled water, Stearic acid, Isopropyl myristate, Lavender oil, Cetyl alcohol, Polyoxyl 40 stearate, Stearyl alcohol, Xanthan gum, Potassium sorbate, Frankincense oil, Myrrh oil, Grapefruit seed extract

PURPOSE

Use: Temporary relief of hot flashes.

KEEP OUT OF REACH OF CHILDREN.

WARNINGS

Warnings: FOR EXTERNAL USE ONLY. Do not use if allergic to any ingredient. Consult a doctor before use for serious conditions, if conditions worsen or persist, or accidental ingestion occurs. If pregnant or nursing, consult a doctor before use. Avoid contact with eyes. Do not use if safety seal is broken or missing.

QUESTIONS

Questions? Call 866.642.2858 Made with care by Uriel, East Troy, WI 53120 www.urielpharmacy.com